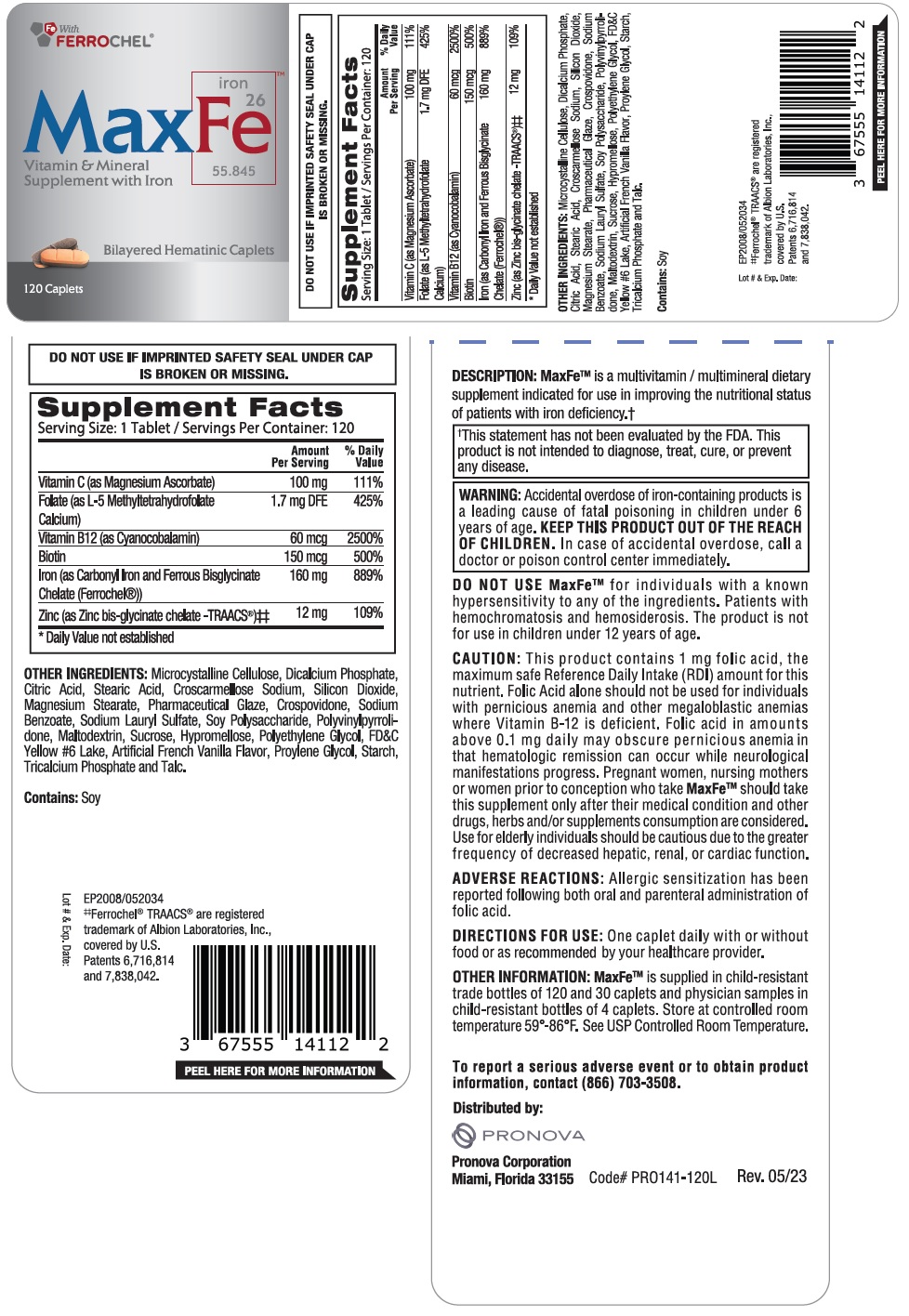 DRUG LABEL: MaxFe
NDC: 67555-141 | Form: TABLET
Manufacturer: Pronova Corporation
Category: other | Type: DIETARY SUPPLEMENT
Date: 20230516

ACTIVE INGREDIENTS: MAGNESIUM ASCORBATE 100 mg/1 1; LEVOMEFOLATE CALCIUM 1 mg/1 1; CYANOCOBALAMIN 60 ug/1 1; BIOTIN 150 ug/1 1; FERROUS BISGLYCINATE 160 mg/1 1; ZINC GLYCINATE 12 mg/1 1
INACTIVE INGREDIENTS: MICROCRYSTALLINE CELLULOSE; ANHYDROUS DIBASIC CALCIUM PHOSPHATE; CITRIC ACID MONOHYDRATE; STEARIC ACID; CROSCARMELLOSE SODIUM; SILICON DIOXIDE; MAGNESIUM STEARATE; SHELLAC; CROSPOVIDONE, UNSPECIFIED; SODIUM BENZOATE; SODIUM LAURYL SULFATE; SOYBEAN COTYLEDON CELL WALL POLYSACCHARIDES; POVIDONE, UNSPECIFIED; MALTODEXTRIN; SUCROSE; HYPROMELLOSE, UNSPECIFIED; POLYETHYLENE GLYCOL, UNSPECIFIED; FD&C YELLOW NO. 6; PROPYLENE GLYCOL; STARCH, RICE; TRICALCIUM PHOSPHATE; TALC

MaxFe

STATEMENT OF IDENTITY

Supplement Facts
Serving Size: 1 Tablet / Servings Per Container: 120
 | Amount; Per Serving | % Daily; Value
Vitamin C (as Magnesium Ascorbate) | 100 mg | 111%
Folate (as L-5 Methyltetrahydrofolate Calcium) | 1.7 mg DFE | 425%
Vitamin B12 (as Cyanocobalamin) | 60 mcg | 2500%
Biotin | 150 mcg | 500%
Iron (as Carbonyl Iron and Ferrous Bisglycinate Chelate (Ferrochel®)) | 160 mg | 889%
Zinc (as Zinc bis-glycinate chelate -TRAACS®)# | 12 mg | 109%
* Daily Value not established

OTHER INGREDIENTS: Microcrystalline Cellulose, Dicalcium Phosphate, Citric Acid, Stearic Acid, Croscarmellose Sodium, Silicon Dioxide, Magnesium Stearate, Pharmaceutical Glaze, Crospovidone, Sodium Benzoate, Sodium Lauryl Sulfate, Soy Polysaccharide, Polyvinylpyrrolidone, Maltodextrin, Sucrose, Hypromellose, Polyethylene Glycol, FD&C Yellow #6 Lake, Artificial French Vanilla Flavor, Propylene Glycol, Starch, Tricalcium Phosphate and Talc.

Contains: Soy

DESCRIPTION: MaxFeTM is a multivitamin / multimineral dietary supplement indicated for use in improving the nutritional status of patients with iron deficiency.†

†This statement has not been evaluated by the FDA. This product is not intended to diagnose, treat, cure, or prevent any disease.

WARNINGS

WARNING: Accidental overdose of iron-containing products is leading a cause of fatal poisoning in children under 6 years of age. KEEP THIS PRODUCT OUT OF REACH OF CHILDREN. In case of accidental overdose, call a doctor or poison control center immediately.

DO NOT USE MAXFeTM for individuals with a known hypersensitivity to any of the ingredients. Patients with hemochromatosis and hemosiderosis. The product is not for use in children under 12 years of age.

CAUTION:

This product contains 1 mg folic acid, the maximum safe Reference Daily Intake (RDI) amount for this nutrient. Folic Acid alone should not be used for individuals with pernicious anemia and other megaloblastic anemias where Vitamin B-12 is deficient. Folic acid in amounts above 0.1 mg daily may obscure pernicious anemia in that hematologic remission can occur while neurological manifestations progress. Pregnant women, nursing mothers or women prior to conception who take MAXFeTM should take this supplement only after their medical condition and other drugs, herbs and/or supplements consumption are considered. Use for elderly individuals should be cautious due to the greater frequency of decreased hepatic, renal, or cardiac function.

ADVERSE REACTIONS: Allergic sensitization has been reported following both oral and parenteral administration of folic acid.

DIRECTIONS FOR USE:

One caplet daily with or without food or as recommended by your healthcare provider.

OTHER INFORMATION:

MAXFeTM is supplied in child-resistant trade bottles of 120 and 30 caplets and physician samples in child-resistant bottles of 4 caplets. Store at controlled room temperature 59°-86°F. See USP Controlled Room Temperature.

To report a serious advent event or to obtain product information, contact (866) 703-3508.

Distributed by:

Pronova Corporation
Miami, Florida 33155

HEALTH CLAIM

Fe With FERROCHEL®

Vitamin & Mineral Supplement with Iron

Bilayered Hematinic Caplets

DO NOT USE IF IMPRINTED SAFETY SEAL UNDER CAP IS BROKEN OR MISSING.

EP2008/052034
#Ferrochel® TRAACS® are registered
trademark of Albion Laboratories, Inc.,
covered by U.S.
Patents 6,716,814
and 7,838,042.